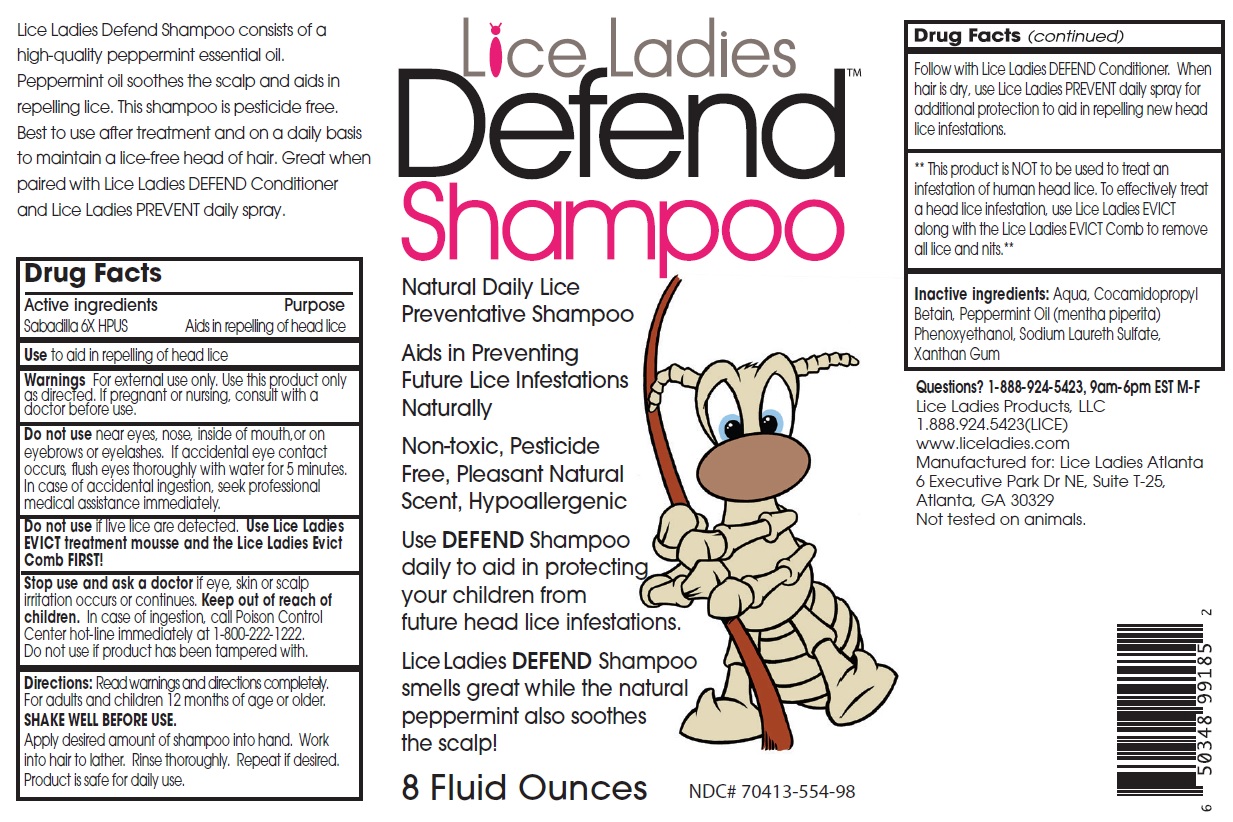 DRUG LABEL: Lice Ladies Defend
NDC: 70413-554 | Form: SHAMPOO
Manufacturer: Lice Ladies Atlanta, LLC
Category: homeopathic | Type: HUMAN OTC DRUG LABEL
Date: 20251110

ACTIVE INGREDIENTS: SCHOENOCAULON OFFICINALE SEED 6 [hp_X]/1 mL
INACTIVE INGREDIENTS: WATER; COCAMIDOPROPYL BETAINE; PEPPERMINT OIL; PHENOXYETHANOL; SODIUM LAURETH-3 SULFATE; XANTHAN GUM

Lice Ladies Defend™ Shampoo

Active ingredients

Sabadilla 6X HPUS

Purpose

Aids in repelling of head lice

Use

to aid in repelling of head lice

Warnings

For external use only. Use this product only as directed. If pregnant or nursing, consult with a doctor before use.

Do not use near eyes, nose, inside of mouth,or on eyebrows or eyelashes. If accidental eye contact occurs, flush eyes thoroughly with water for 5 minutes. In case of accidental ingestion, seek professional medical assistance immediately.

Do not use if live lice are detected. Use Lice Ladies EVICT treatment mousse and the Lice Ladies Evict Comb FIRST!

Stop use and ask a doctor if eye, skin or scalp irritation occurs or continues.

Keep out of reach of children. In case of ingestion, call Poison Control Center hot-line immediately at 1-800-222-1222.
Do not use if product has been tampered with.

Directions:

Read warnings and directions completely.
For adults and children 12 months of age or older.
SHAKE WELL BEFORE USE.
Apply desired amount of shampoo into hand. Work into hair to lather. Rinse thoroughly. Repeat if desired. Product is safe for daily use.
Follow with Lice Ladies DEFEND Conditioner. When hair is dry, use Lice Ladies PREVENT daily spray for additional protection to aid in repelling new head lice infestations.

** This product is NOT to be used to treat an infestation of human head lice. To effectively treat a head lice infestation, use Lice Ladies EVICT along with the Lice Ladies EVICT Comb to remove all lice and nits.**

Inactive ingredients:

Aqua, Cocamidopropyl Betaine, Peppermint Oil (mentha piperita), Phenoxyethanol, Sodium Laureth Sulfate, Xanthan Gum

Questions?

1-888-924-5423, 9am-6pm EST M-F

Natural Daily Lice Preventative Shampoo

Aids in Preventing Future Lice Infestations Naturally

Non-toxic, Pesticide Free, Pleasant Natural Scent, Hypoallergenic

Use DEFEND Shampoo daily to aid in protecting your children from future head lice infestations.

Lice Ladies DEFEND shampoo smells great while the natural peppermint also soothes the scalp!

Lice Ladies Products, LLC
1.888.924.5423(LICE)
www.liceladies.com
Manufactured for: Lice Ladies Atlanta
6 Executive Park Dr NE, Suite T-25,
Atlanta, GA 30329
Not tested on animals.

Lice Ladies Defend Shampoo consists of a high-quality peppermint essential oil. Peppermint oil soothes the scalp and aids in repelling lice. This shampoo is pesticide free. Best to use after treatment and on a daily basis to maintain a lice-free head of hair. Great when paired with Lice Ladies DEFEND Conditioner and Lice Ladies PREVENT daily spray.